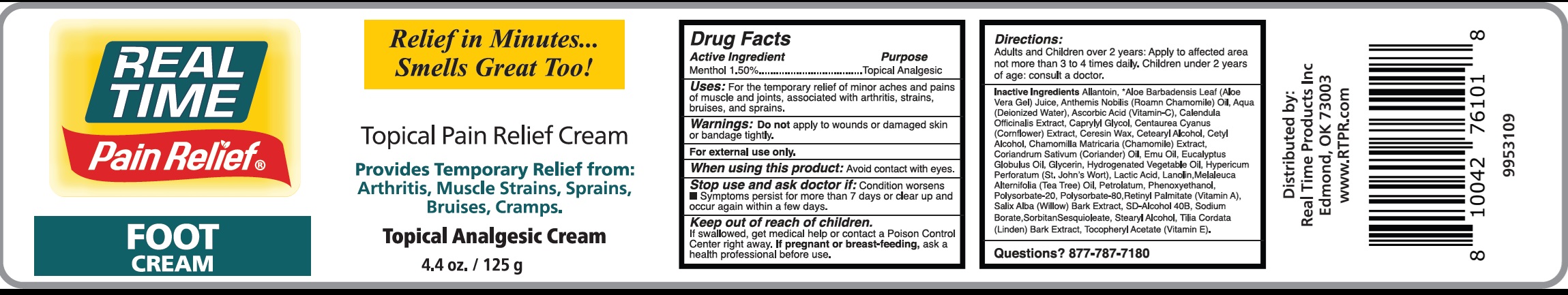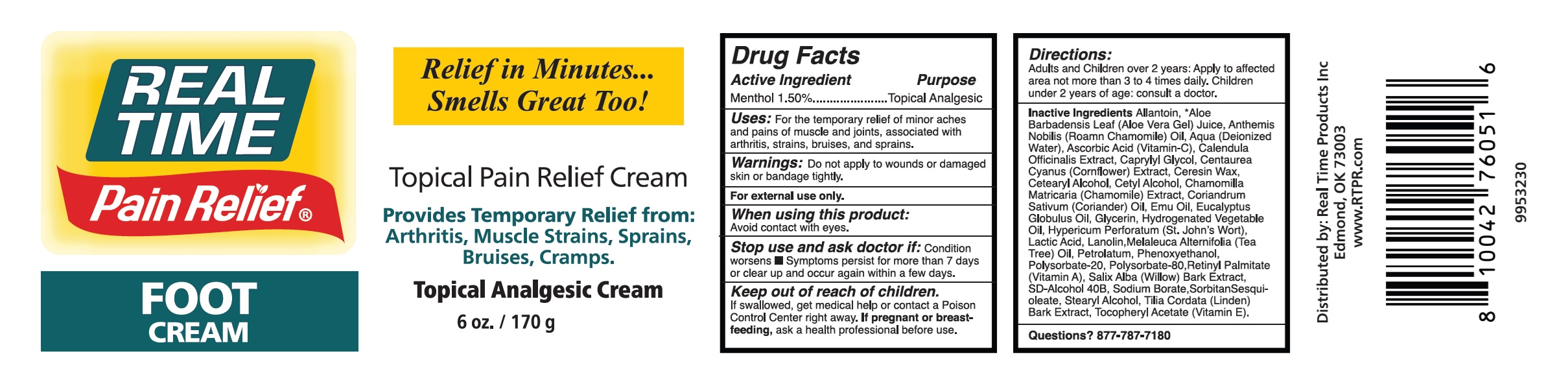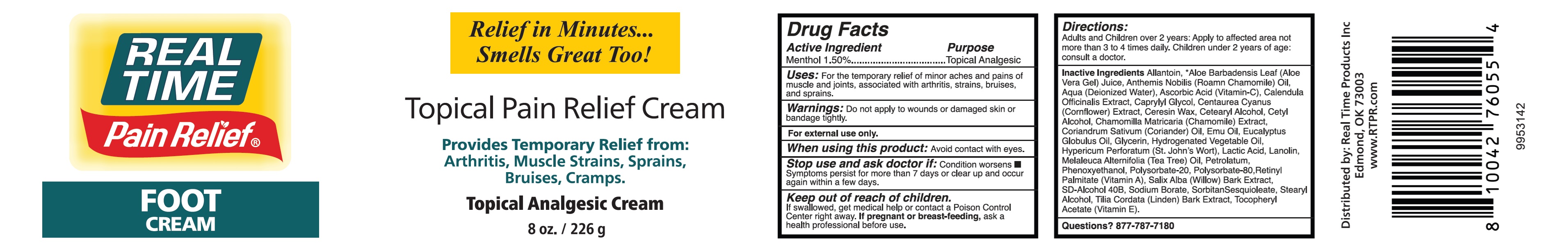 DRUG LABEL: Real Time Pain Relief Foot
NDC: 84573-515 | Form: CREAM
Manufacturer: Real Time Products Inc.
Category: otc | Type: HUMAN OTC DRUG LABEL
Date: 20240724

ACTIVE INGREDIENTS: MENTHOL 15 mg/1 g
INACTIVE INGREDIENTS: ALLANTOIN; ALOE VERA LEAF; WATER; ASCORBIC ACID; CALENDULA OFFICINALIS FLOWER; CAPRYLYL GLYCOL; CERESIN; CETOSTEARYL ALCOHOL; CETYL ALCOHOL; CHAMOMILE; CORIANDER; EMU OIL; EUCALYPTUS OIL; GLYCERIN; ST. JOHN'S WORT; LACTIC ACID, UNSPECIFIED FORM; LANOLIN; MELALEUCA ALTERNIFOLIA LEAF; PETROLATUM; PHENOXYETHANOL; POLYSORBATE 20; POLYSORBATE 80; VITAMIN A; SALIX ALBA BARK; SODIUM BORATE; SORBITAN SESQUIOLEATE; STEARYL ALCOHOL; .ALPHA.-TOCOPHEROL

Real Time Pain Relief Foot Cream

Active Ingredient

Menthol 1.50%

Purpose

Topical Analgesic

Uses:

For the temporary relief of minor aches and pains of muscle and joints, associated with arthritis, strains, bruises, and sprains.

Warnings:

Do notapply to wounds or damaged skin or bandage tightly.

For external use only.

When using this product:

Avoid contact with eyes.

Stop use and ask doctor if:

Condition worsens

- Symptoms persist for more than 7 days or clear up and occur again within a few days.

Keep out of reach of children.

If swallowed, get medical help or contact a Poison Control Center right away.

If pregnant or breast-feeding,

ask a health professional before use.

Directions:

Adults and Children over 2 years: Apply to affected area not more than 3 to 4 times daily. Children under 2 years of age: consult a doctor.

Inactive Ingredients

Allantoin, *Aloe Barbadensis Leaf (Aloe Vera Gel) Juice, Anthemis Nobilis (Roamn Chamomile) Oil, Aqua (Deionized Water), Ascorbic Acid (Vitamin-C), Calendula Officinalis Extract, Caprylyl Glycol, Centaurea Cyanus (Cornflower) Extract, Ceresin Wax, Cetearyl Alcohol, Cetyl Alcohol, Chamomilla Mantricaria (Chamomile) Extract, Coriandrum Sativum (Coriander) Oil, Emu Oil, Eucalyptus Globulus Oil, Glycerin, Hydrogenated Vegetable Oil, Hypericum Perforatum (St.John's Wort), Lactic Acid, Lanolin, Melaleuca Alternifolia (Tea Tree) Oil, Petrolatum, Phenoxyethanol, Polysorbate-20, Polysorbate-80, Retinyl Palmitate (Vitamin A), Salix Alba (Willow) Bark Extract, SD-Alcohol 40B, Sodium Borate, SorbitanSesquioleate, Stearyl Alcohol, Tilia Cordata (Linden) Bark Extract, Tocopheryl Acetate (Vitamin E).

Questions?

877-787-7180